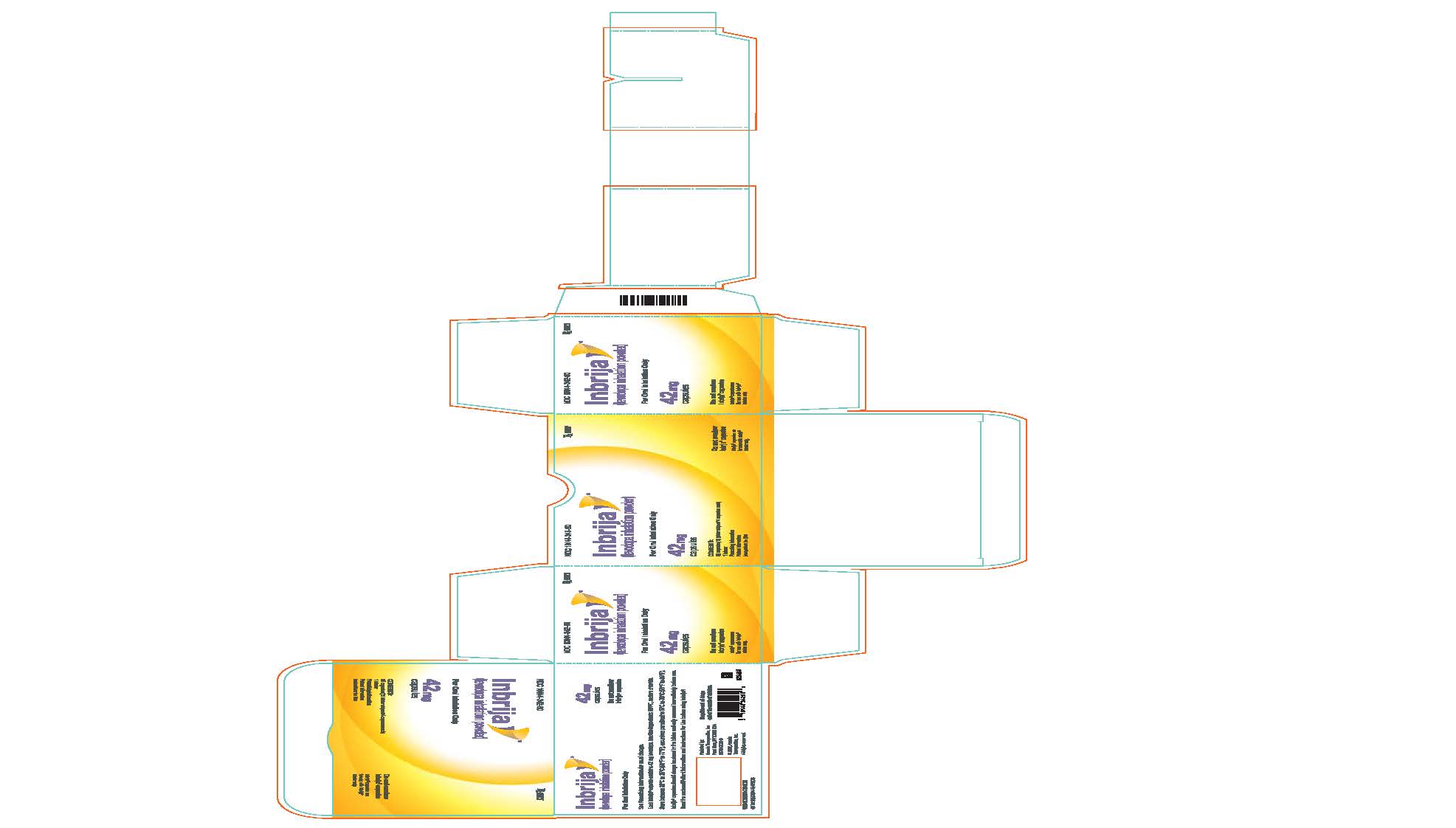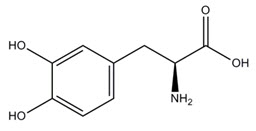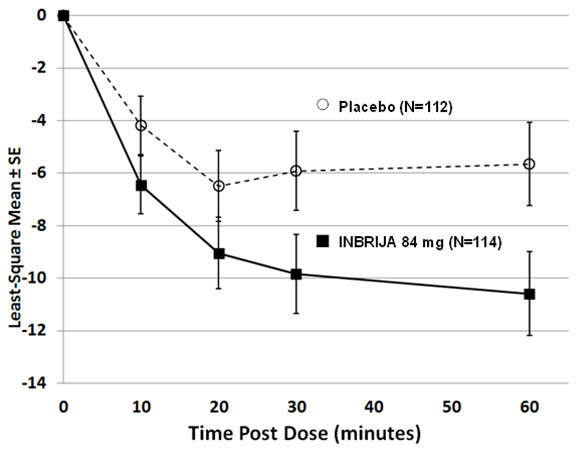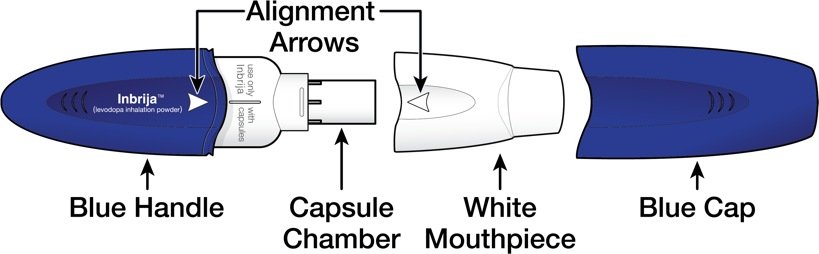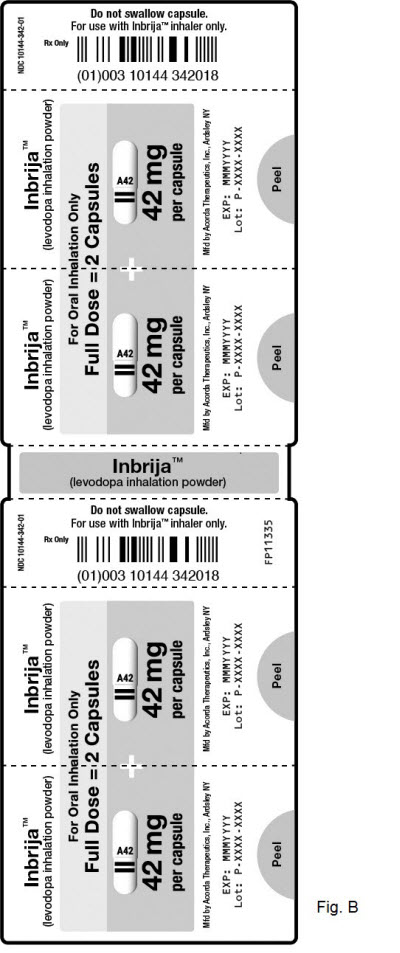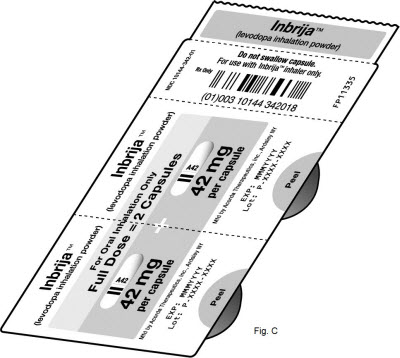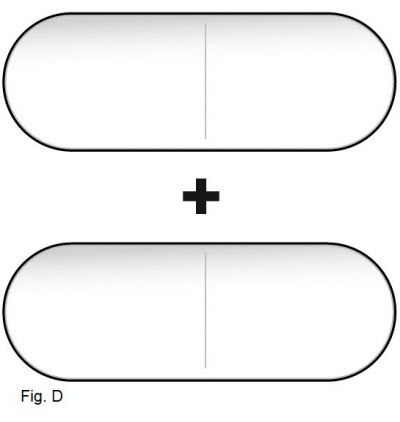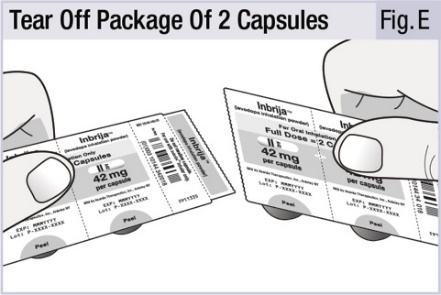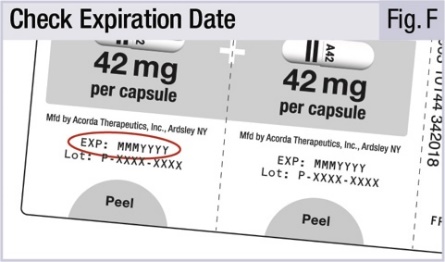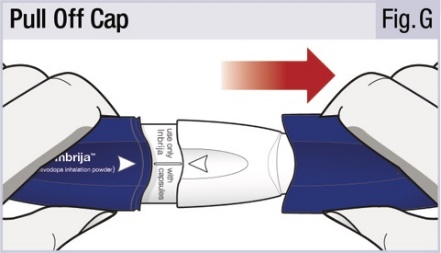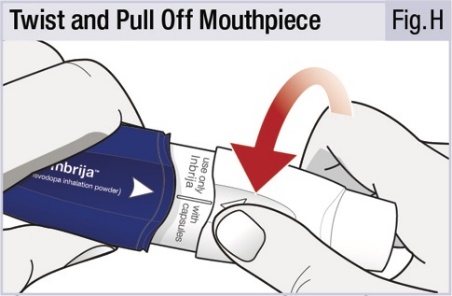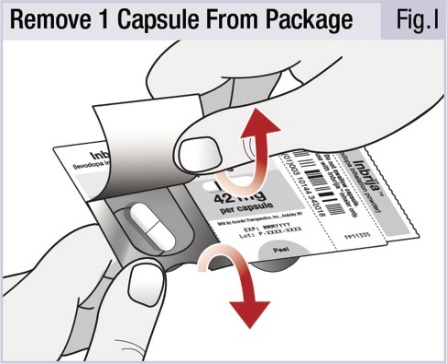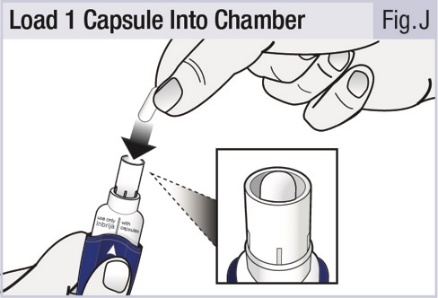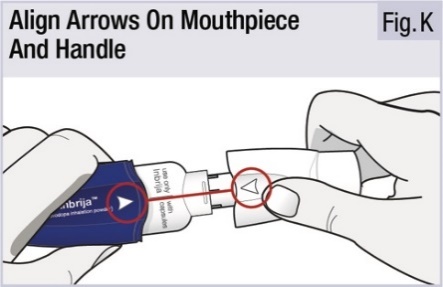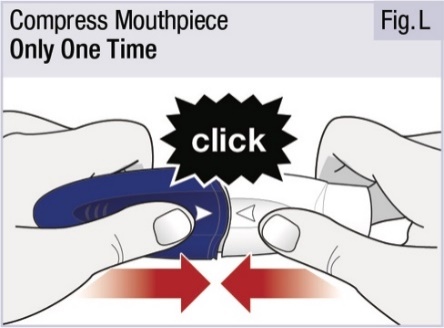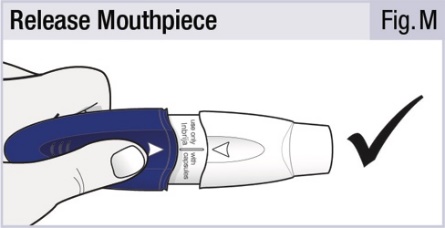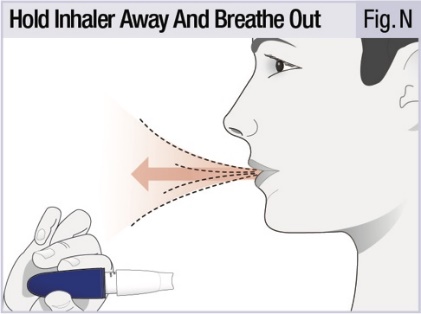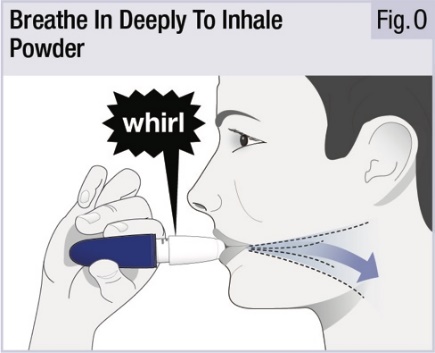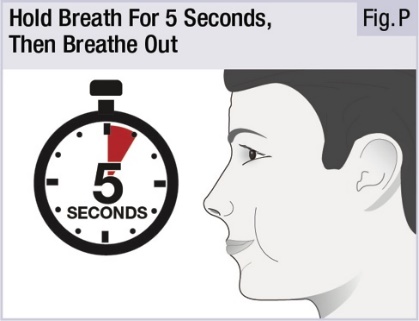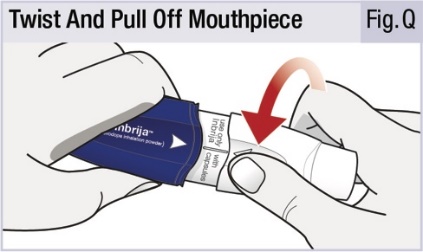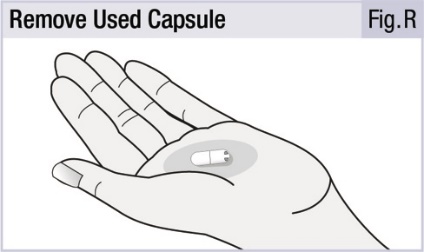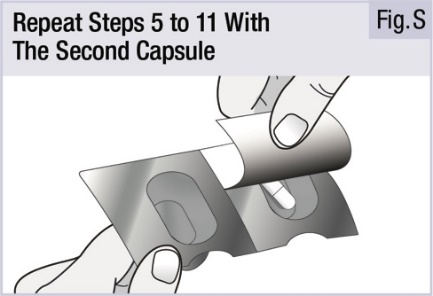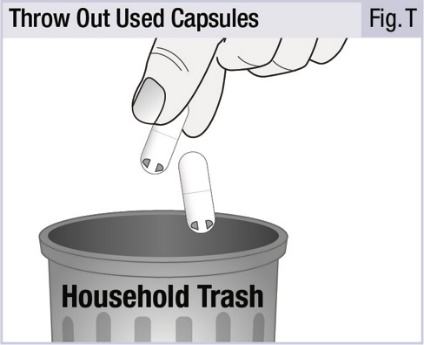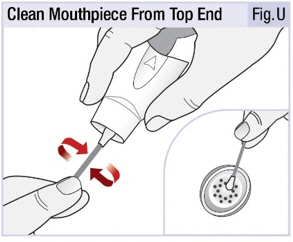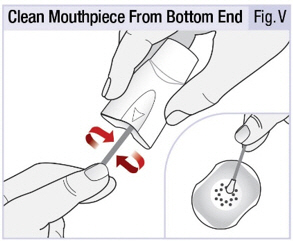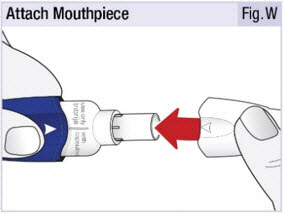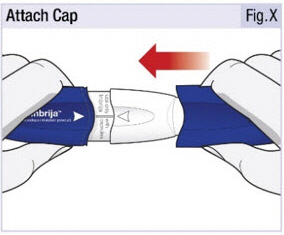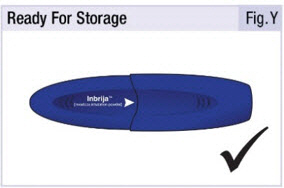 DRUG LABEL: Inbrija
NDC: 10144-342 | Form: CAPSULE
Manufacturer: Merz Pharmaceuticals, LLC
Category: prescription | Type: HUMAN PRESCRIPTION DRUG LABEL
Date: 20260116

ACTIVE INGREDIENTS: LEVODOPA 42 mg/1 1
INACTIVE INGREDIENTS: DIPALMITOYLPHOSPHATIDYLCHOLINE, DL-; SODIUM CHLORIDE

HIGHLIGHTS OF PRESCRIBING INFORMATION

These highlights do not include all the information needed to use INBRIJA safely and effectively. See full prescribing information for INBRIJA.
INBRIJA® (levodopa inhalation powder), for oral inhalation use
Initial U.S. Approval: 1970

1 INDICATIONS AND USAGE

INBRIJA is an aromatic amino acid indicated for the intermittent treatment of OFF episodes in patients with Parkinson's disease treated with carbidopa/levodopa (1)

2 DOSAGE AND ADMINISTRATION

- For oral inhalation only. DO NOT swallow INBRIJA capsules. Only use INBRIJA capsules with the INBRIJA inhaler (2.1)
- Inhale the contents of two INBRIJA capsules (84 mg) as needed for OFF symptoms, up to 5 times daily (2.2)
- The maximum dose per OFF period is 84 mg, and the maximum recommended daily dosage of INBRIJA is 420 mg (2.2)

3 DOSAGE FORMS AND STRENGTHS

Inhalation powder: INBRIJA capsules contain 42 mg levodopa for use with the INBRIJA inhaler (3)

4 CONTRAINDICATIONS

INBRIJA is contraindicated in patients currently taking a nonselective monoamine oxidase (MAO) inhibitor or who have recently (within 2 weeks) taken a nonselective MAO inhibitor (4, 7.1)

5 WARNINGS AND PRECAUTIONS

- May cause falling asleep during activities of daily living (5.1)
- Avoid sudden discontinuation or rapid dose reduction to reduce the risk of withdrawal-emergent hyperpyrexia and confusion (5.2)
- Hallucinations/exacerbation of psychosis may occur. Patients with a major psychotic disorder should not be treated with INBRIJA (5.3, 7.2)
- Impulse Control Disorders: consider dose reduction or stopping INBRIJA (5.4)
- May cause or exacerbate dyskinesia: adjustment of levodopa therapy may be considered, including stopping INBRIJA (5.5)
- Not recommended in patients with asthma, COPD, or other chronic underlying lung disease (5.6)

6 ADVERSE REACTIONS

The most common adverse reactions (incidence ≥ 5% and higher than placebo) were cough, nausea, upper respiratory tract infection, and sputum discolored (6.1)

To report SUSPECTED ADVERSE REACTIONS, contact Acorda Therapeutics, Inc. at 1-800-367-5109 or FDA at 1-800-FDA-1088 or www.fda.gov/medwatch.

7 DRUG INTERACTIONS

- Monitor patients on MAO-B inhibitors for orthostatic hypotension (7.1)
- Dopamine D2 antagonists, isoniazid, and iron salts: May reduce the effectiveness of INBRIJA (7.2, 7.3)

8 USE IN SPECIFIC POPULATIONS

Pregnancy: Based on animal data, may cause fetal harm (8.1)

FULL PRESCRIBING INFORMATION

1 INDICATIONS AND USAGE

INBRIJA is indicated for the intermittent treatment of OFF episodes in patients with Parkinson's disease treated with carbidopa/levodopa.

2 DOSAGE AND ADMINISTRATION

INBRIJA capsules are for oral inhalation only and should be used only with the INBRIJA inhaler.

2.1 Important Administration Instructions

INBRIJA capsules are for oral inhalation only and should be used only with the INBRIJA inhaler. INBRIJA capsules must not be swallowed as the intended effect will not be obtained. INBRIJA capsules should be stored in their blister package and only removed immediately before use [see How Supplied/Storage and Handling (16.2)] .

2.2 Recommended Dosage

INBRIJA should be taken when symptoms of an OFF period start to return.

The recommended dosage of INBRIJA is oral inhalation of the contents of two 42 mg capsules (84 mg) as needed, up to 5 times a day. The maximum dose per OFF period is 84 mg, and the maximum daily dosage is 420 mg. INBRIJA has been shown to be effective only in combination with carbidopa/levodopa [see Indications and Usage (1)].

3 DOSAGE FORMS AND STRENGTHS

INBRIJA (levodopa inhalation powder) consists of INBRIJA capsules and the INBRIJA inhaler. INBRIJA capsules contain 42 mg dry powder formulation of levodopa in a white capsule with two black color bands, and "A42" printed on one side.

4 CONTRAINDICATIONS

INBRIJA is contraindicated in patients currently taking a nonselective monoamine oxidase (MAO) inhibitor (e.g., phenelzine and tranylcypromine) or who have recently (within 2 weeks) taken a nonselective MAO inhibitor. Hypertension can occur if these drugs are used concurrently [see Drug Interactions (7.1)].

5 WARNINGS AND PRECAUTIONS

5.1 Falling Asleep During Activities of Daily Living and Somnolence

Patients treated with levodopa, the active ingredient in INBRIJA, have reported falling asleep while engaged in activities of daily living, including the operation of motor vehicles, which sometimes resulted in accidents. Although many of these patients reported somnolence, some reported no warning signs (sleep attack) and believed that they were alert immediately prior to the event. Some of these events have been reported more than 1 year after the initiation of treatment.

Prescribers should reassess patients for drowsiness or sleepiness. Prescribers should also be aware that patients may not acknowledge drowsiness or sleepiness until directly questioned about drowsiness or sleepiness during specific activities.

Before initiating treatment with INBRIJA, advise patients about the potential to develop drowsiness and ask about factors that may increase the risk for somnolence with INBRIJA such as the concomitant use of sedating medications and the presence of sleep disorders. Consider discontinuing INBRIJA in patients who report significant daytime sleepiness or episodes of falling asleep during activities that require active participation (e.g., conversations, eating, etc.).

If treatment with INBRIJA continues, patients should be advised not to drive and to avoid other activities that might result in harm if the patients become somnolent. There is insufficient information to establish that dose reduction will eliminate episodes of falling asleep while engaged in activities of daily living.

5.2 Withdrawal-Emergent Hyperpyrexia and Confusion

A symptom complex that resembles neuroleptic malignant syndrome (characterized by elevated temperature, muscular rigidity, altered consciousness, and autonomic instability), with no other obvious etiology, has been reported in association with rapid dose reduction, withdrawal of, or changes in dopaminergic therapy.

5.3 Hallucinations/Psychosis

In placebo-controlled trials [see Clinical Studies (14)], hallucinations were reported in less than 2% of patients treated with INBRIJA. Hallucinations may be responsive to reducing levodopa therapy. Hallucinations may be accompanied by confusion, insomnia, and excessive dreaming. Abnormal thinking and behavior may present with one or more symptoms, including paranoid ideation, delusions, hallucinations, confusion, psychotic-like behavior, disorientation, aggressive behavior, agitation, and delirium.

Because of the risk of exacerbating psychosis, patients with a major psychotic disorder should ordinarily not be treated with INBRIJA. In addition, medications that antagonize the effects of dopamine used to treat psychosis may exacerbate the symptoms of Parkinson's disease and may decrease the effectiveness of INBRIJA [see Drug Interactions (7.2)].

5.4 Impulse Control/Compulsive Behaviors

Patients treated with INBRIJA can experience intense urges to gamble, increased sexual urges, intense urges to spend money, binge eating, and/or other intense urges, and the inability to control these urges while taking one or more of the medications that increase central dopaminergic tone. In some cases, although not all, these urges were reported to have stopped when the dose was reduced or the medication was discontinued.

Because patients may not recognize these behaviors as abnormal, it is important for prescribers to specifically ask patients or their caregivers about the development of new or increased gambling urges, sexual urges, uncontrolled spending or other urges while being treated with INBRIJA. Consider stopping the medication if a patient develops such urges while taking INBRIJA.

5.5 Dyskinesia

INBRIJA may cause or exacerbate dyskinesias. If troublesome dyskinesias occur, prescribers may need to consider stopping treatment with INBRIJA and/or adjusting the patient's daily medications for the treatment of Parkinson's disease. In Study 1, 4% of patients treated with INBRIJA 84 mg reported dyskinesia, compared with 1% for patients on placebo [see Adverse Reactions (6.1)] .

5.6 Bronchospasm in Patients with Lung Disease

Because of the risk of bronchospasm, use of INBRIJA in patients with asthma, COPD, or other chronic underlying lung disease is not recommended.

In a double-blind, placebo-controlled, crossover clinical study, 25 otherwise healthy subjects with mild or moderate asthma on a stable regimen of asthma medication received placebo or INBRIJA 84 mg every 4 hours for a total of three doses. Cough was the most frequent adverse reaction, reported by 60% of subjects following administration of INBRIJA and 0% following administration of placebo. Following administration of INBRIJA, 10 subjects (40%) had temporary reductions from baseline (between 15% and 59%) for FEV1; 4 of these subjects also had a reduction in FEV1 following administration of placebo. Subjects with a reduction in FEV1 remained asymptomatic and did not require rescue treatment.

5.7 Glaucoma

INBRIJA may cause increased intraocular pressure in patients with glaucoma. Monitor patients for increased intraocular pressure during therapy with INBRIJA.

5.8 Laboratory Test Abnormalities

Abnormalities in laboratory tests may include elevations of liver function tests such as alkaline phosphatase, AST, ALT, lactic dehydrogenase (LDH), and bilirubin. Abnormalities in blood urea nitrogen (BUN), hemolytic anemia and positive direct antibody test have also been reported.

Patients taking levodopa or carbidopa-levodopa may have increased levels of catecholamines and their metabolites in plasma and urine giving false positive results suggesting the diagnosis of pheochromocytoma in patients on levodopa and carbidopa-levodopa.

6 ADVERSE REACTIONS

The following serious adverse reactions are discussed below and elsewhere in the labeling:

- Falling Asleep During Activities of Daily Living and Somnolence [see Warnings and Precautions (5.1)]
- Withdrawal-Emergent Hyperpyrexia and Confusion [see Warnings and Precautions (5.2)]
- Hallucinations/Psychosis [see Warnings and Precautions (5.3)]
- Impulse Control/Compulsive Behaviors [see Warnings and Precautions (5.4)]
- Dyskinesia [see Warnings and Precautions (5.5)]
- Bronchospasm in Patients with Lung Disease [see Warnings and Precautions (5.6)]
- Glaucoma [see Warnings and Precautions (5.7)]

6.1 Clinical Trials Experience

Because clinical trials are conducted under widely varying conditions, adverse reaction rates observed in the clinical trials of a drug cannot be directly compared to rates in the clinical trials of another drug and may not reflect the rates observed in clinical practice.

Adverse Reactions in Study 1

Table 1 lists the adverse reactions that occurred in at least 2% of patients with Parkinson's disease who were treated with INBRIJA 84 mg and higher than placebo for OFF periods in Study 1 [see Clinical Studies (14)]. Study 1 was a double-blind, placebo-controlled study, in which 114 patients received INBRIJA 84 mg (two 42 mg capsules) for an average of 2 doses per day, to a maximum of 5 times a day, and 112 patients received placebo. INBRIJA-treated patients were 45-82 years of age (mean 63.5 years of age) and were predominantly male (72%) and white (94%). All patients were also treated with oral carbidopa/levodopa. The most common adverse reactions (≥ 5% and higher than placebo) in Study 1 were cough, nausea, upper respiratory tract infection, and sputum discolored.

Table 1: Adverse Reactions at an Incidence ≥2% and More Frequent with INBRIJA than with Placebo in Study 1
Adverse Reactions | INBRIJA 84 mg N=114 % | Placebo N=112 %
Respiratory, thoracic and mediastinal disorders
Cough | 15 | 2
Sputum discolored | 5 | 0
Nasal discharge discoloration | 2 | 0
Oropharyngeal pain | 2 | 0
Gastrointestinal disorders
Nausea | 5 | 3
Vomiting | 3 | 0
Infections and infestations
Upper respiratory tract infection | 6 | 3
Nasopharyngitis | 3 | 2
Bronchitis/pneumonia | 2 | 0
Nervous system disorders
Dyskinesia | 4 | 1
Headache | 2 | 0
Injury, poisoning and procedural complications
Fall | 3 | 2
Laceration | 2 | 0
Skin abrasion | 2 | 0
General disorders and administration site conditions
Chest discomfort | 2 | 0
Investigations
Blood bilirubin increased | 2 | 0
Red blood cell count decreased | 2 | 0
Musculoskeletal and connective tissue disorders
Pain in extremity | 2 | 1
Psychiatric disorders
Insomnia | 2 | 1
Vascular disorders
Orthostatic hypotension/blood pressure decreased | 2 | 0

Adverse Reactions Leading to Discontinuation in Study 1

In Study 1, 6 of 114 patients (5%) in the INBRIJA 84 mg group and 3 of 112 patients (3%) in the placebo group discontinued because of adverse reactions. The most common of these adverse reactions was cough, which lead to discontinuation in 2% of patients in the INBRIJA 84 mg group and none in the placebo group.

6.2 Postmarketing Experience

The following adverse reaction has been identified during post approval use of INBRIJA. Because adverse reactions are reported voluntarily from a population of uncertain size, it is not always possible to reliably estimate their frequency or establish a causal relationship to drug exposure: sensation of choking immediately following administration.

7 DRUG INTERACTIONS

7.1 Monoamine Oxidase (MAO) Inhibitors

The use of nonselective MAO inhibitors with INBRIJA is contraindicated [see Contraindications (4)] . Discontinue use of any nonselective MAO inhibitors at least two weeks prior to initiating INBRIJA.

The use of selective MAO-B inhibitors with INBRIJA may be associated with orthostatic hypotension. Monitor patients who are taking these drugs concurrently.

7.2 Dopamine D2 Receptor Antagonists and Isoniazid

Dopamine D2 receptor antagonists (e.g., phenothiazines, butyrophenones, risperidone, metoclopramide) and isoniazid may reduce the effectiveness of levodopa. Monitor patients for worsening Parkinson's symptoms.

7.3 Iron Salts

Iron salts or multivitamins containing iron salts can form chelates with levodopa and consequently reduce the bioavailability of levodopa.

8 USE IN SPECIFIC POPULATIONS

8.1 Pregnancy

Risk Summary

There are no adequate data on the developmental risk associated with the use of INBRIJA in pregnant women. In animal studies, carbidopa/levodopa has been shown to be developmentally toxic (including teratogenic effects) [see Data]. In the U.S. general population, the estimated background risk of major birth defects and miscarriage in clinically recognized pregnancies is 2-4% and 15-20%, respectively. The background risk of major birth defects and miscarriage for the indicated population is unknown.

Data

Animal Data

When administered to pregnant rabbits throughout organogenesis, carbidopa/levodopa caused both visceral and skeletal malformations in rabbits. No teratogenic effects were observed when carbidopa/levodopa was administered to pregnant mice throughout organogenesis.

There was a decrease in the number of live pups delivered by rats receiving carbidopa/levodopa during organogenesis.

8.2 Lactation

Risk Summary

The prolactin-lowering action of dopamine suggests that levodopa may interfere with lactation, although there are limited data on the effects of levodopa on milk production in lactating women.

Levodopa has been detected in human milk. There are no adequate data on the effects of levodopa on the breastfed infant. The developmental and health benefits of breastfeeding should be considered along with the mother's clinical need for INBRIJA and any potential adverse effects on the breastfed infant from INBRIJA or from the underlying maternal condition.

8.4 Pediatric Use

Safety and effectiveness in pediatric patients have not been established.

8.5 Geriatric Use

Of the Parkinson's disease patients in Study 1 who took INBRIJA 84 mg, 49% (n=56) were 65 years of age and older and 51% (n=58) were under 65 years of age. Of these patients, the following age-related differences in adverse reactions were reported in patients 65 years of age and older vs. in patients under 65 years of age, respectively: cough 25% vs. 5%; upper respiratory tract infection 11% vs. 2%; nausea 7% vs. 3%; vomiting 4% vs. 2%; pain in the extremities 4% vs. 0%; and discolored nasal discharge 4% vs. 0%.

10 OVERDOSAGE

Based on the limited available information, the acute symptoms of carbidopa/levodopa overdosage can be expected to arise from dopaminergic overstimulation. Using more than one dose (84 mg) to treat the same OFF period may result in CNS disturbances, with an increasing risk for cardiovascular disturbance (e.g., hypotension, tachycardia) and increased risk for new or worsening psychiatric problems at higher doses.

Reports of rhabdomyolysis and transient renal insufficiency suggest that levodopa overdosage may give rise to systemic complications.

Monitor patients and provide supportive care. Patients should receive electrocardiographic monitoring for the development of arrhythmias; if needed, appropriate antiarrhythmic therapy should be given. The possibility that the patient may have taken other drugs, increasing the risk of drug interactions (especially catechol-structured drugs) should be taken into consideration.

11 DESCRIPTION

INBRIJA consists of a dry powder formulation of levodopa for oral inhalation with the INBRIJA inhaler. The inhalation powder is packaged in white hypromellose capsules.

Each capsule contains a spray-dried powder of 42 mg levodopa active ingredient with 1,2-dipalmitoyl-sn-glycero-3-phosphocholine (DPPC) and sodium chloride.

The active component of INBRIJA is levodopa, an aromatic amino acid. Its chemical name is (2S)-2-amino-3-(3,4-dihydroxyphenyl) propanoic acid and its structural formula is:

Levodopa has a molecular weight of 197.19 g/mol and molecular formula C9H11NO4. Levodopa is a white to slightly off-white powder and is readily soluble in formic acid, slightly soluble in water, and practically insoluble in ethanol and diethyl ether; it dissolves in dilute hydrochloric acid.

The INBRIJA inhaler is a plastic device with a blue body, blue cap, and white mouthpiece used for inhaling INBRIJA powder.

The INBRIJA inhaler is breath-actuated by the patient. Under standardized in vitro testing conditions, the INBRIJA inhaler delivered 36.1 mg of levodopa (emitted dose) for the 42 mg capsule from the mouthpiece. No significant difference in emitted dose was observed when varying the flow rate and volume from 20 liters per minute/1L up to 90 liters per minute/2L. Peak inspiratory flow rates (PIFR) achievable through the INBRIJA inhaler were evaluated in 24 adult patients with mild to moderate Parkinson's disease. The mean PIFR was 64 L/min (range 39–98 L/min) for patients in the ON state and 57 L/min (range 29–98 L/min) in the OFF state.

12 CLINICAL PHARMACOLOGY

12.1 Mechanism of Action

Levodopa, the metabolic precursor of dopamine, crosses the blood-brain barrier and presumably is converted to dopamine in the brain. This is thought to be the mechanism whereby levodopa relieves symptoms of Parkinson's disease.

12.2 Pharmacodynamics

There are no relevant data on the pharmacodynamic effects of INBRIJA.

12.3 Pharmacokinetics

In the presence of carbidopa, the pharmacokinetics of levodopa are dose-proportional in healthy subjects taking up to 84 mg of INBRIJA. In the presence of carbidopa, the terminal elimination half-life (t1/2) of levodopa following a single administration of INBRIJA 84 mg was 2.3 hours.

Absorption

After a single dose of INBRIJA 84 mg (two 42 mg capsules), the median Tmax for plasma levodopa was approximately 0.5 hours (range 0.17–2.00 hours). In fasted healthy volunteers the bioavailability of levodopa from INBRIJA was approximately 70% relative to immediate-release oral levodopa tablets. The dose-normalized Cmax of levodopa from INBRIJA is approximately 50% of that following immediate-release oral tablets.

Distribution

Apparent volume of distribution (Vz/F) was 168 L for INBRIJA 84 mg.

Metabolism and Elimination

Levodopa is extensively metabolized, and the two major metabolic pathways are decarboxylation by dopa decarboxylase and O-methylation by catechol-O-methyltransferase (COMT).

Specific Populations

Geriatric Population

Clinical studies specifically designed to analyze the effects of age on the pharmacokinetics of levodopa were not conducted with INBRIJA.

Male and Female Patients

After a single dose administration of INBRIJA 84 mg, the body-weight adjusted Cmax and AUC0-24 were similar between women and men. No adjustment in dosage is required based on sex.

Hepatic/ Renal Impairment

INBRIJA has not been studied in patients with hepatic or renal impairment.

Smokers

In a pharmacokinetic study following a single administration of INBRIJA 84 mg dose in the presence of carbidopa, levodopa exposure (AUC and Cmax) in smokers (N=25) and non-smokers (N=31) were similar.

13 NONCLINICAL TOXICOLOGY

13.1 Carcinogenesis, Mutagenesis, Impairment of Fertility

Carcinogenesis

In rats, oral administration of carbidopa/levodopa for two years resulted in no evidence of carcinogenicity.

Mutagenesis

Studies to assess the potential mutagenic or clastogenic effects of levodopa have not been conducted.

Impairment of Fertility

In reproduction studies in rats, oral administration of carbidopa/levodopa resulted in no effects on fertility.

14 CLINICAL STUDIES

The efficacy and safety of INBRIJA for the treatment of OFF episodes in patients with Parkinson's disease treated with oral carbidopa/levodopa was evaluated in a 12-week, randomized, placebo-controlled, double-blind study (Study 1; NCT02240030).

Study 1:

In Study 1, a total of 114 patients were treated with INBRIJA 84 mg (two 42 mg capsules), and 112 patients received placebo. Study medication could be administered up to five times a day. At baseline, patients had at least 2 hours of OFF time per day, and carbidopa/levodopa medication did not exceed 1600 mg levodopa per day. The mean UPDRS Part III scores at screening in the ON state were 14.9 for patients randomized to INBRIJA 84 mg and 16.1 for patients randomized to placebo. The UPDRS part III is designed to assess the severity of the cardinal motor findings (e.g., tremor, rigidity, bradykinesia, postural instability) in patients with Parkinson's disease.

The primary endpoint was the change in Unified Parkinson's Disease Rating Scale (UPDRS) Part III motor score from pre-dose OFF state to 30 minutes post-dose, measured at Week 12. The average use of INBRIJA 84 mg or placebo was approximately 2 doses per day. At Week 12, the reduction in UPDRS Part III motor score for INBRIJA 84 mg, compared to placebo at 30 minutes post-dose, were -9.8 and -5.9, respectively (See Table 2 and Figure 1). The proportion of patients who returned to an ON state and sustained that ON through 60 minutes post-dose was 58% for INBRIJA 84 mg and 36% for placebo (p=0.003).

Table 2: Mean Change in UPDRS Part III Motor Score at 30 minutes post-dose (INBRIJA 84 mg) for the Intent-to-Treat Population at Week 12 [Treatment group least-squares mean change is a model-based population estimate; the pre-dose and post-dose means are descriptive statistics.]
Treatment | Pre-dose (OFF) UPDRS Part III Motor Score (mean) | Post-dose UPDRS Part III Motor Score (mean) | Mean Change 30 minutes post-dose [Least-squares mean.] , [Negative numbers indicate improvement as compared with the baseline value.] | Difference from Placebo (95% confidence interval) | p-value
Placebo | 32.1 | 25.3 | -5.9 | — | —
INBRIJA 84 mg | 29.0 | 19.3 | -9.8 | -3.92 (-6.84, -1.00) | 0.009

Figure 1: Least-squares Mean Change in UPDRS Part III Motor Score After Administration of INBRIJA 84 mg vs. Placebo (at Week 12)

Study 2

The effect of INBRIJA on pulmonary function was evaluated in patients with Parkinson's disease treated with oral carbidopa/levodopa in a 12 month, randomized, controlled, open-labeled study (Study 2: NCT02352363). A total of 271 patients were treated with INBRIJA 84 mg (two 42 mg capsules), and 127 patients with Parkinson's disease in a control group were observed on their regular oral medication regimen for the treatment of Parkinson's disease. Patients with chronic obstructive pulmonary disease (COPD), asthma, or other chronic respiratory disease within the last 5 years were excluded [see Warnings and Precautions (5.6)]. Pulmonary function was assessed by spirometry every 3 months in both groups. After 12 months, the average reduction in the forced expiratory volume in 1 second (FEV1) from baseline was the same in both groups (-0.1 L).

16 HOW SUPPLIED/STORAGE AND HANDLING

16.1 How Supplied

INBRIJA 42 mg contains foil blister strips of INBRIJA (levodopa inhalation powder) white capsules with two black bands on the body and "A42" in black on the cap, and one INBRIJA inhaler.

- Carton containing 4 INBRIJA capsules (1 blister card containing 4 capsules) and 1 INBRIJA inhaler: NDC 10144-342-04
- Carton containing 12 INBRIJA capsules (3 blister cards containing 4 capsules each) and 1 INBRIJA inhaler: NDC 10144-342-12
- Carton containing 60 INBRIJA capsules (15 blister cards containing 4 capsules each) and 1 INBRIJA inhaler: NDC 10144-342-60
- Carton containing 92 INBRIJA capsules (23 blister cards containing 4 capsules each) and 1 INBRIJA inhaler: NDC 10144-342-92

INBRIJA inhaler consists of a blue cap, blue handle with "INBRIJA" imprinted on it, and white mouthpiece covering the capsule chamber.

16.2 Storage and Handling

Store in a dry place between 20°C to 25°C (68°F to 77°F), excursions permitted to 15°C to 30°C (59°F to 86°F).

INBRIJA capsules should always be stored in the blister packaging and only removed immediately before use. INBRIJA capsules should not be stored inside the INBRIJA inhaler.

INBRIJA capsules should be used only with the INBRIJA inhaler.

The INBRIJA inhaler should not be used to administer any other medicines.

17 PATIENT COUNSELING INFORMATION

Advise the patient to read the FDA-approved patient labeling (Patient Information and Instructions for Use).

Instructions for Administering INBRIJA

It is important for patients to understand how to correctly administer INBRIJA. It is recommended that patients be instructed in the proper administration of INBRIJA prior to use [see Dosage and Administration (2.1)] .

Patients should be counseled to take a dose of INBRIJA when the return of their Parkinson's symptoms (OFF periods) first occur [see Dosage and Administration (2.2)] .

Instruct patients to read the Instructions for Use before using INBRIJA. Remind patients that INBRIJA capsules should only be administered via the INBRIJA inhaler and the INBRIJA inhaler should not be used for administering other medications. Remind patients that the contents of INBRIJA capsules are for oral inhalation only and must not be swallowed. Instruct patients to keep INBRIJA capsules in their sealed blister packaging and to remove each INBRIJA capsule immediately before using [see Dosage and Administration (2.1)] .

Remind patients they need to orally inhale the contents of two capsules to take a full dose. They should not take more than 5 doses of INBRIJA in one day. Instruct patients they should not take more than one dose (2 capsules) per OFF period [see Dosage and Administration (2.2)] .

Lung Disease

Ask patients to report whether they develop asthma, COPD, or other chronic lung diseases, since INBRIJA is not recommended in patients with these conditions [see Warnings and Precautions (5.6)] .

Cough/Sensation of Choking

Inhalation of INBRIJA can lead to coughing or a sensation of choking at the time of administration [see Warnings and Precautions (5.6), and Adverse Reactions (6.1, 6.2)] .

Discoloration of Body Fluids

Patients should be advised that dark color may appear in bodily fluids (saliva, sputum, urine, or sweat) when using INBRIJA [see Adverse Reactions (6.1)] .

Falling Asleep

Advise patients that certain side effects such as sleepiness and dizziness may affect some patients' ability to drive and operate machinery safely. Advise patients of the possible additive sedative effects when taking other CNS depressants in combination with INBRIJA [see Warnings and Precautions (5.1)] .

Impulse Control Disorder

Inform patients of the potential for experiencing Impulse Control Disorder: patients may experience intense urges to gamble, increased sexual urges, and other intense urges and the inability to control these urges while taking one or more of the medications that increase central dopaminergic tone, that are generally used for the treatment of Parkinson's disease [see Warnings and Precautions (5.4)] .

Dyskinesia

Instruct patients to notify their healthcare provider if abnormal involuntary movements appear or get worse during treatment with INBRIJA [see Warnings and Precautions (5.5)] .

Hypotension and Syncope

Advise patients that while they are on levodopa therapy, including INBRIJA, that they may develop orthostatic hypotension with or without symptoms such as dizziness, nausea, syncope, and sweating [see Adverse Reactions (6.1)] . Advise patients to rise slowly after sitting or lying down, especially if they have been doing so for a prolonged period.

Iron Salts

Inform patients that iron salts or multivitamins containing iron salts can reduce the bioavailability of levodopa [see Drug Interactions (7.3)].

Pregnancy and Breastfeeding

Instruct patients to notify their physicians if they become pregnant or intend to become pregnant during therapy [see Use in Specific Populations (8.1)] .

Instruct patients to notify their physicians if they intend to breastfeed or are breastfeeding an infant [see Use in Specific Populations (8.2)] .

Marketed by:
Acorda Therapeutics, Inc.
Pearl River, NY 10965 USA
2212342WPI-0

PATIENT INFORMATION
INBRIJA® (in-BRIH-jah)
(levodopa inhalation powder)
for oral inhalation use

What is INBRIJA?
INBRIJA is an inhaled prescription levodopa medicine used to treat the return of Parkinson's symptoms (known as OFF episodes) in people with Parkinson's disease who are treated with carbidopa-levodopa medicines. It does not replace the regular carbidopa-levodopa medicines.
It is not known if INBRIJA is safe or effective in children.

Do not use INBRIJA if you:

- take another medicine called a nonselective monoamine oxidase inhibitor (MAOI), such as phenelzine and tranylcypromine, or have taken a nonselective MAOI within the last 2 weeks. Ask your healthcare provider or pharmacist if you are not sure if you take an MAOI.

Before you use INBRIJA, tell your healthcare provider about all of your medical conditions, including if you:

- have asthma, chronic obstructive pulmonary disease (COPD), or any chronic lung disease.
- have daytime sleepiness from a sleep disorder or get drowsy or sleepy without warning or take a medicine to help you sleep.
- feel dizzy, nauseated, sweaty, or faint when you stand up from sitting or lying down.
- have a history of abnormal movement (dyskinesia).
- have or have had a mental health problem such as hallucinations or psychosis.
- have urges that you are unable to control (for example, gambling, increased sexual urges, intense urges to spend money, or binge eating).
- have glaucoma.
- are pregnant or plan to become pregnant. It is not known if INBRIJA will harm your unborn baby.
- are breastfeeding or plan to breastfeed. Levodopa the medicine in INBRIJA can pass into your breastmilk. It is not known if it can harm your baby.

Tell your healthcare provider about all the medicines you take, including prescription and over-the-counter medicines, vitamins, and herbal supplements.
Using INBRIJA and certain other medicines may affect each other and cause serious side effects.
Especially tell your healthcare provider if you take:

- MAO-B inhibitors
- dopamine D2 receptor antagonists, including phenothiazines, butyrophenones, risperidone, and metoclopramide, or isoniazid
- iron salts or multivitamins with iron salts

Ask your healthcare provider or pharmacist for a list of these medicines if you are not sure.
Know the medicines you take. Keep a list of them to show your healthcare provider and pharmacist each time you get a new medicine.

How should I use INBRIJA?

- See the step-by-step Instructions for Use that come with your INBRIJA prescription.
- Your healthcare provider should show you the right way to use INBRIJA before you start using it.
- INBRIJA is for oral inhalation use only.
- Do not swallow INBRIJA capsules.
- Do not open INBRIJA capsules.
- Only use INBRIJA capsules with the INBRIJA inhaler. Do not use the INBRIJA inhaler to take any other medicine.
- You must be taking a daily Parkinson's disease medicine that contains carbidopa and levodopa before you start taking INBRIJA. You must not stop taking your daily Parkinson's medicine. INBRIJA does not replace your daily medicine.
- Use INBRIJA exactly as prescribed.
- The dose of INBRIJA is 2 capsules. Do not take more than 1 dose (2 capsules) for any OFF period.
- Take an INBRIJA dose as soon as you feel Parkinson's symptoms start to return.
- Do not take more than 5 doses of INBRIJA in 1 day.

What should I avoid while using INBRIJA?

- Do not drive, operate machinery, or do other activities until you know how INBRIJA affects you. INBRIJA can cause sleepiness and falling asleep suddenly as late as 1 year after you start treatment.

What are the possible side effects of INBRIJA?
INBRIJA can cause serious side effects including:

- falling asleep during normal daily activities. INBRIJA may cause you to fall asleep while you are doing normal daily activities such as driving a car, doing physical tasks, using hazardous machinery, talking with other people, or eating.
  - You could fall asleep without being drowsy or without warning. If you become drowsy while using INBRIJA, you should not drive or do activities where you need to be alert for your safety or the safety of others.
  - Your chances of falling asleep while doing normal activities while using INBRIJA are greater if you take other medicines that cause drowsiness. Tell your healthcare provider if you take medicines that can make you sleepy such as sleep medicines, antidepressants, or antipsychotics.
- withdrawal-emergent hyperpyrexia and confusion. INBRIJA may cause a problem that can happen in people who suddenly lower their dose, stop using, or change their dose of INBRIJA. Symptoms may include:

- fever
- stiff muscles

- confusion
- changes in breathing and heartbeat

- low blood pressure. People on INBRIJA may also develop low blood pressure (hypotension) that can happen without or with the following symptoms:

- dizziness
- nausea

- fainting
- sweating

Get up slowly after sitting or lying down, especially if you have been sitting or lying down for a long time. Tell your healthcare provider if you have any of these symptoms.

- hallucinations and other psychosis. INBRIJA can cause or worsen psychotic symptoms including:
  - hallucinations (seeing or hearing things that are not real)
  - confusion, disorientation, or disorganized thinking
  - trouble sleeping (insomnia)
  - dreaming a lot
  - being overly suspicious or feeling people want to harm you (paranoid ideation)
  - believing things that are not real (delusional beliefs)
  - acting aggressive
  - feeling agitated or restless
  If you have hallucinations or any of these changes, talk with your healthcare provider.
- unusual urges. Some people using medicines like INBRIJA for Parkinson's have had unusual urges such as gambling, binge eating or eating that you cannot control (compulsive), compulsive shopping and sexual urges. If you or your family members notice that you are having unusual urges, talk to your healthcare provider.
- uncontrolled, sudden body movements (dyskinesia). INBRIJA may cause or worsen movements you cannot control in your face, tongue, or other body parts. Tell your healthcare provider if this happens. Your treatment with INBRIJA may need to be stopped or your other medicines for Parkinson's may need to be changed.
- bronchospasm. People with lung disease such as asthma, COPD, or other lung diseases have a risk of wheezing or difficulty breathing (bronchospasm) after inhaling INBRIJA. If you have these symptoms, stop taking INBRIJA and call your healthcare provider or go to the nearest hospital emergency room right away.
- increased eye pressure. INBRIJA may cause increased intraocular pressure in people with glaucoma. Your healthcare provider should check your eyes while you are using INBRIJA.
- changes in certain lab values. INBRIJA may cause changes in certain lab tests, including liver tests.

The most common side effects of INBRIJA include:

- cough
- upper respiratory tract infection
- nausea
- change in the color of your saliva or spit

Other side effects of INBRIJA:

- sensation of choking right after use

These are not all the possible side effects with INBRIJA. Call your doctor for medical advice about side effects. You may report side effects to FDA at 1-800-FDA-1088.

How should I store INBRIJA?

- Store the inhaler and capsules in a dry place at room temperature between 68°F to 77°F (20°C to 25°C).
- Keep capsules in their foil (blister) packages until just before you are ready to use them.
- Do not store capsules inside the inhaler for a future dose.
- Keep the inhaler and capsules dry.
- Throw out the inhaler after all capsules in the carton have been used. Use the new inhaler that comes with your prescription refill.

Keep INBRIJA and all medicines out of the reach of children.

General information about the safe and effective use of INBRIJA
Medicines are sometimes prescribed for purposes other than those listed in the Patient Information leaflet. Do not use INBRIJA for a condition for which it was not prescribed. Do not give INBRIJA to other people even if they have the same symptoms that you have. It may harm them.
You can ask your pharmacist or healthcare provider for information about INBRIJA that is written for health professionals.

What are the ingredients in INBRIJA?
Active ingredient: levodopa
Inactive ingredients: 1,2-dipalmitoyl-sn-glycero-3-phosphocholine (DPPC), sodium chloride.
For more information, go to www.INBRIJA.com, or call 1-800-367-5109.

This Patient Information has been approved by the U.S. Food and Drug Administration

Issued: 12/2022

INSTRUCTIONS FOR USE

INBRIJA® (in-BRIH-jah)
(levodopa inhalation powder)
For Oral Inhalation Only

Read and follow these instructions before you start using INBRIJA and each time you get a refill. There may be new information. This leaflet does not take the place of talking to your healthcare provider about your medical condition or treatment.

Important Information about using INBRIJA

- Do not swallow INBRIJA capsules
- INBRIJA capsules should only be used with the INBRIJA inhaler and inhaled through your mouth (oral inhalation)

Overview:

A complete dose is 2 capsules.

You will load 1 capsule into the inhaler and breathe in (inhale). Then, you will remove the used capsule and load a second capsule into the inhaler and breathe in. Do not swallow INBRIJA capsules.

- Each carton contains 1 INBRIJA inhaler and capsules in sealed foil packages. When you open a new carton, always use the new inhaler supplied.
- Do not use capsules after the expiration date printed on the package.
- Do not load 2 capsules at the same time.
- Throw out all used capsules immediately after use.
- Throw out the inhaler after all capsules in the carton have been used.
- Make sure your hands are clean and dry when using the inhaler and capsules.

If you have any questions, ask your healthcare provider or pharmacist. If you have problems using INBRIJA, or if your INBRIJA inhaler becomes lost or damaged and you need a replacement, contact INBRIJA support at 1-800-367-5109. Then, call your healthcare provider for treatment instructions until you receive your replacement inhaler.

Parts of your INBRIJA Inhaler
(see Figure A)

Capsules

(see Figure B)
Each carton includes strips of 4 capsules.

(see Figure C)
Prepare and take a total of 2 capsules.
Take each capsule 1 at a time for a full dose.

(see Figure D)
Full Dose = 2 Capsules

Prepare Your Dose
Step 1. Gather Supplies
Find a clean and dry surface.
Make sure your hands are clean and dry.
Get inhaler and strip of capsules.
Tear off package of 2 capsules (see Figure E).

Step 2. Check Expiration
Check the expiration date on the package (see Figure F).

Step 3. Remove Blue Cap
Pull the cap straight off (see Figure G).
Place the cap to the side. You will need it later to store the inhaler.

Step 4. Twist Off White Mouthpiece
Twist and pull off the mouthpiece to separate it from the handle (see Figure H).
Place the mouthpiece and inhaler on a clean and dry surface.

Step 5. Remove 1 Capsule From Package
Carefully peel back the foil and take out 1 capsule (see Figure I).
Do not try to push the capsule through the back of the foil package.
Only remove 1 capsule at a time, and just before use.
Do not use any capsule that looks crushed, damaged or wet. Throw it away and get a new capsule.

Step 6. Load Capsule
Hold the inhaler upright using the handle.
Drop 1 capsule into the opening of the capsule chamber (see Figure J).
Do not try to load 2 capsules at the same time.

Step 7. Attach White Mouthpiece
Line up the white arrows on the handle and mouthpiece (see Figure K).

Firmly push the mouthpiece and handle together until you hear a click. This punctures the capsule (see Figure L).

Release the mouthpiece. The mouthpiece will spring back and stay attached (see Figure M).
Your inhaler is now ready to use.
Do not push the handle and mouthpiece together more than 1 time. This may damage the capsule, and you may not get your full dose. If this happens throw the capsule away in your household trash and start over at Step 5.
Make sure the mouthpiece is securely attached and will not fall off before moving to step 8.

Take Your Dose

Step 8. Breathe Out (Exhale)
Stand or sit with your head and chest upright.
Hold the inhaler level and away from your mouth (see Figure N).
Breathe out completely (see Figure N).
Do not breathe into mouthpiece.

Step 9. Breathe In Deeply (Inhale)
While keeping the inhaler level, close your lips firmly around the mouthpiece (see Figure O).
Take in a deep, comfortable breath until your lungs feel full. This normally takes several seconds.
As you breathe in, you will hear and feel the capsule "whirl" (spin). The whirl means the inhaler is working and you are getting your medicine.
If you cough or stop your dose, start again from the beginning of Step 8 using the same capsule.

Important: If you did not hear or feel the capsule "whirl" while inhaling you may need to take a deeper, longer breath or may need to clean the mouthpiece. Refer to Step 14 – Clean Mouthpiece. Start again from the beginning of Step 8 using the same capsule.

Step 10. Hold Breath, Then Breathe Out
Take the inhaler out of your mouth and hold your breath for 5 seconds (see Figure P).
Then breathe out.

Step 11. Remove Capsule From Inhaler
Twist and pull off the mouthpiece (see Figure Q) and take out the used capsule (see Figure R).

Step 12. Dose With 2nd Capsule
Repeat Steps 5 to 11 with the second capsule to finish the full dose (see Figure S).

Dispose and Store

Step 13. Throw Out Used Capsules Throw out used capsules in the household trash (see Figure T).

Step 14. Clean Mouthpiece
It is normal for some powder to remain in or on the inhaler. To avoid powder buildup, clean the powder off of the mouthpiece holes using a circular motion with a new dry cotton swab as needed.
First, clean the holes from the top end of the mouthpiece (see Figure U).
Next, clean the holes from the bottom end of the mouthpiece (see Figure V).
You can also use a dry tissue to wipe the outside of the mouthpiece, as needed.
Do not clean any other parts of the inhaler.
Do not rinse the mouthpiece or get the inhaler wet.

Step 15. Store Inhaler
Make sure there are no capsules in the inhaler before you store it.
Attach the mouthpiece to the handle by pushing until you hear a click (see Figure W).

Attach the cap over the mouthpiece (see Figure X).
Your inhaler is now ready to store (see Figure Y).

INBRIJA Storage, Cleaning and Disposal

Storing the Inhaler and Capsules

- Store the inhaler and capsules in a dry place at room temperature from 68°F to 77°F (20 to 25°C).
- Keep capsules inside their foil (blister) packages until just before you are ready to use them.
- Do not store capsules in the inhaler for a future dose.
- Keep the inhaler and capsules dry.
- Throw out the inhaler after all capsules in the carton have been used. Use the new inhaler that comes with your prescription refill.
- Keep INBRIJA and all medicines out of reach of children.

Cleaning the Inhaler

- It is normal for some powder to remain in or on the inhaler.
- If needed, to avoid powder buildup, you may use a dry cotton swab or a dry tissue to wipe the inside or outside of the mouthpiece.

Disposing of the Inhaler and Capsules

- Throw out all used capsules in your household trash.
- After all capsules in the carton have been used, throw out the inhaler and use a new carton containing a new inhaler and capsules.

This Instructions for Use has been approved by the U.S. Food and Drug Administration Rev: 12/2022

Marketed by:
Acorda Therapeutics, Inc.
Pearl River, NY 10965 USA

Inbrija® is a trademark of Acorda Therapeutics, Inc.

©2022 Acorda Therapeutics, Inc. All rights reserved.

U.S. Patent Nos. 7182961, 8404276, 8545878, 8586093, 8685442, 8945612, 9155699, 9393210 and RE43711

2212342MFPI-0

PRINCIPAL DISPLAY PANEL - 42 mg Capsule Blister Pack Carton

NDC 10144-342-60
Rx ONLY

Inbrija®
(levodopa inhalation powder)

For Oral Inhalation Only

42 mg
capsules

CONTENTS:
60 capsules (15 blister
strips of 4 capsules each)
1 inhaler
Prescribing Information
Patient Information
Instructions for Use

Do not swallow
Inbrija® capsules

Inbrija® capsules are
for use with Inbrija®
inhaler only.